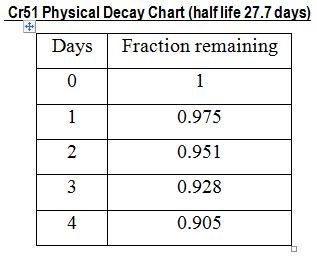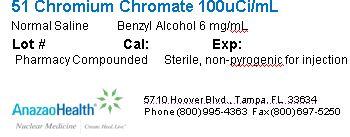 DRUG LABEL: Sodium Chromate 51
NDC: 51808-101 | Form: SOLUTION
Manufacturer: AnazaoHealth Corporation
Category: prescription | Type: HUMAN PRESCRIPTION DRUG LABEL
Date: 20120619

ACTIVE INGREDIENTS: CHROMIUM CR-51 1 mCi/5 mL
INACTIVE INGREDIENTS: BENZYL ALCOHOL 30 mg/5 mL; SODIUM CHLORIDE

Sodium Chromate 51

Per your order, we have compounded Chromium 51 as a sterile intravenous injectable dispensed as 1 mL in a 5 mL vial. The characteristics of this preparation are described below

DESCRIPTION

AnazaoHealth’s compounded Cr-51 vial is a sterile, non-pyrogenic diagnostic radiopharmaceutical that consists up to 1 mCi of Cr-51 (precalibrated) in a volume up to 5 mL normal saline and 6 mg/mL benzyl alcohol.

INDICATIONS AND USAGE

Cr51 is indicated for use in determining red blood cell volume or mass, studying red blood cell survival time (in conditions such as hemolytic anemia), and evaluating blood loss

Mechanism of Action

The chromium in this agent is present as the dianionic chromate ion in which form it appears to bind to the red blood cell in two steps, initially by a rapid but reversible attachment to the cell membrane followed by a slower nearly irreversible binding to intracellular hemoglobin and reduction to the anionic state. It has been suggested that the slow rate of uptake is dependent on the rate at which chromate can penetrate the cell membrane. Binding is maintained until the red blood cells are sequestered by the spleen or until elution of the chromium occurs into the plasma. The chromium is then readily excreted mainly in the urine. Once liberated by elution or erythrocyte senescence, chromium 51 is not available for relabeling of red cells.

In normal individuals the erythrocyte survival half-time T ½ as measured by the chromium 51 "random labeling" technique, generally ranges between 25 and 35 days. This apparent short survival time, when compared to the 120 day life span of the red blood cells, is due to the elution of chromium from the cells and to cell damage that probably occurs during the process of withdrawing them from the body and labeling. Subnormal T ½ may be indicative of blood toss, sequestration of red blood cells by the spleen, or shortened cell viability, as occurs In hemolytic anemia

CONTRAINDICATIONS

There are no known contraindications for this preparation

DOSAGE AND ADMINISTRATION

- The suggested dose range in the average patient (70kg) is:
  Determination of red blood cell volume or mass-0.37 to 1.11 megabecquerels (10 to 30 microcuries).
- Study of red blood cell survival time-5.55 megabecquerels (150 microcuries).
- Evaluation of blood loss-7.40 megabecquerels (200 microcuries)

Figure 1

PACKAGE LABEL.PRINCIPAL DISPLAY PANEL

Figure 2